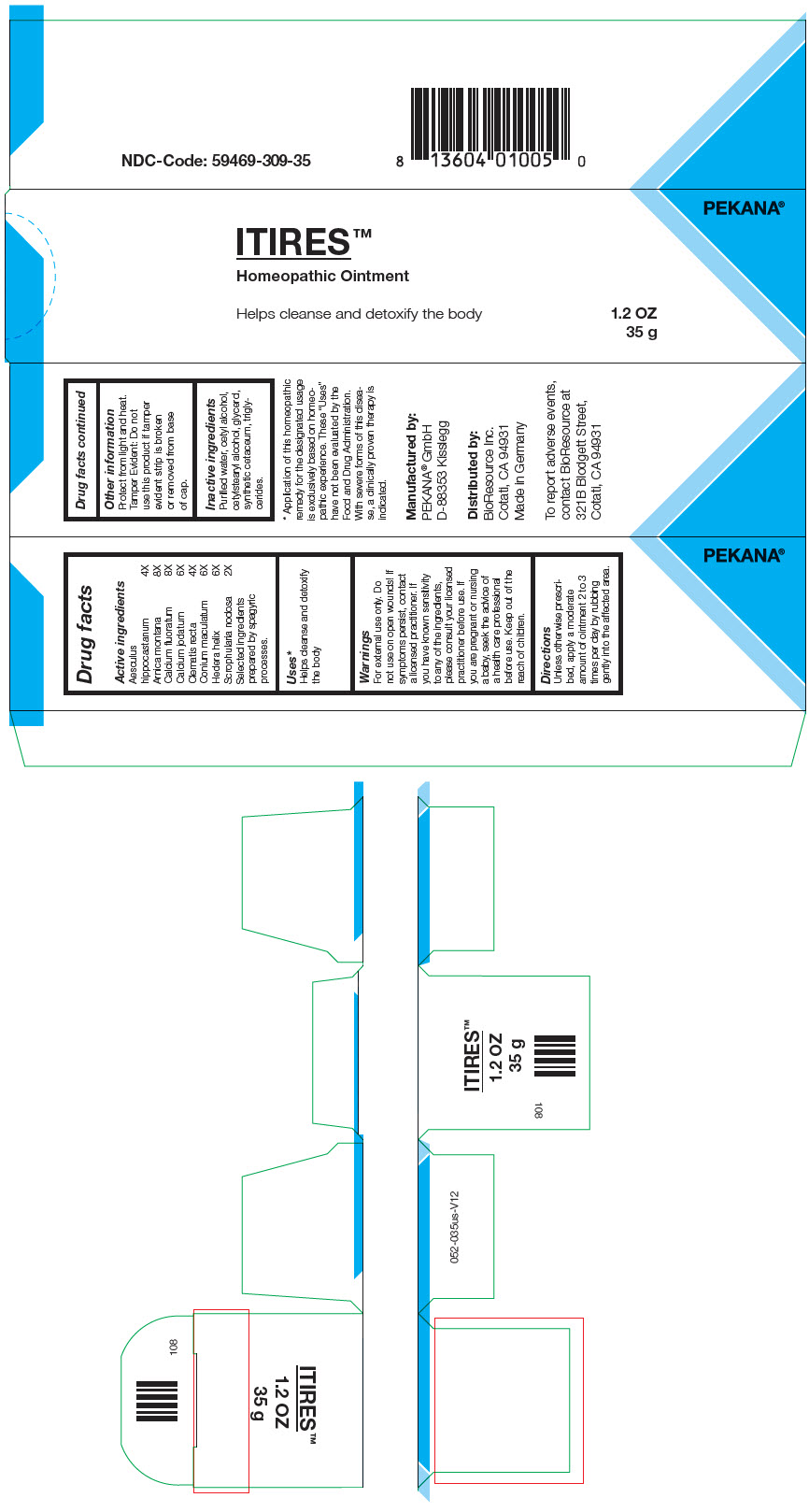 DRUG LABEL: ITIRES
NDC: 59469-309 | Form: OINTMENT
Manufacturer: PEKANA Naturheilmittel GmbH
Category: homeopathic | Type: HUMAN OTC DRUG LABEL
Date: 20221223

ACTIVE INGREDIENTS: Arnica montana Root 8 [hp_X]/35 g; CALCIUM FLUORIDE 8 [hp_X]/35 g; CALCIUM IODIDE 6 [hp_X]/35 g; Clematis recta Flowering Top 4 [hp_X]/35 g; SCROPHULARIA NODOSA WHOLE 2 [hp_X]/35 g; Conium maculatum Flowering Top 6 [hp_X]/35 g; HORSE CHESTNUT 4 [hp_X]/35 g; Hedera helix Flowering Twig 6 [hp_X]/35 g
INACTIVE INGREDIENTS: MEDIUM-CHAIN TRIGLYCERIDES; CETOSTEARYL ALCOHOL; Cetyl Alcohol; SPERMACETI; GLYCERIN; WATER; Alcohol

ITIRES™

Drug facts

Active ingredients
Aesculus hippocastanum | 4X
Arnica montana | 8X
Calcium fluoratum | 8X
Calcium jodatum | 6X
Clematis recta | 4X
Conium maculatum | 6X
Hedera helix | 6X
Scrophularia nodosa | 2X

Selected ingredients prepared by spagyric processes.

Uses [Application of this homeopathic remedy for the designated usage is exclusively based on homeopathic experience. These "Uses" have not been evaluated by the Food and Drug Administration. With severe forms of this disease, a clinically proven therapy is indicated.]

PURPOSE

Helps cleanse and detoxify the body

Warnings

For external use only. Do not use on open wounds! If symptoms persist, contact a licensed practitioner. If you have known sensitivity to any of the ingredients, please consult your licensed practitioner before use. If you are pregnant or nursing a baby, seek the advice of a health care professional before use.

Keep out of the reach of children.

Directions

Unless otherwise prescribed, apply a moderate amount of ointment 2 to 3 times per day by rubbing gently into the affected area.

Other information

Protect from light and heat.

Tamper Evident

Do not use this product if tamper evident strip is broken or removed from base of cap.

Inactive ingredients

Purified water, cetyl alcohol, cetylstearyl alcohol, glycerol, synthetic cetaceum, triglycerides.

Manufactured by:
PEKANA® GmbH
D-88353 Kisslegg

Distributed by:
BioResource Inc.
Cotati, CA 94931

PRINCIPAL DISPLAY PANEL - 35 g Tube Box

PEKANA®

ITIRES™
Homeopathic Ointment

Helps cleanse and detoxify the body

1.2 OZ
35 g